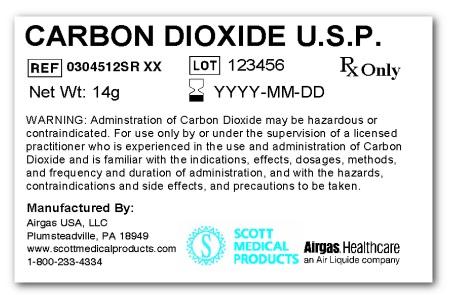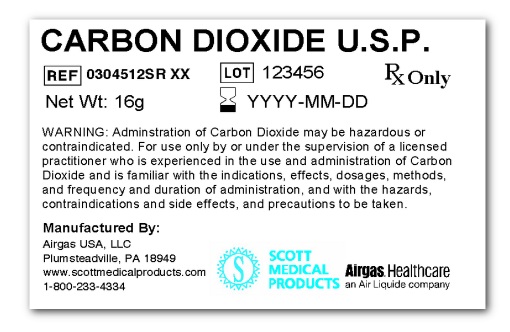 DRUG LABEL: Carbon Dioxide
NDC: 82605-001 | Form: GAS
Manufacturer: AIRGAS THERAPEUTICS LLC
Category: prescription | Type: HUMAN PRESCRIPTION DRUG LABEL
Date: 20251030

ACTIVE INGREDIENTS: CARBON DIOXIDE 1 g/1 g

Carbon Dioxide

PACKAGE LABEL

CARBON DIOXIDE, UN1013
DO NOT REMOVE THIS PRODUCT LABEL
Non-Flammable Gas 2
835148 (10/04)
Rx only CAUTION: Federal law prohibits dispensing without a prescription.
WARNING: Administration of Carbon Dioxide may be hazardous or contraindicated. For use by or under the supervision of a licensed practitioner who is experienced in the use and administration of Carbon Dioxide and is familiar with the indications, effects, dosages, methods, and frequency and duration of administration, and with the hazards, contraindications and side effects, and the precautions to be taken.
WARNING: HIGH PRESSURE LIQUID AND GAS. CAN CAUSE RAPID SUFFOCATION. CAN INCREASE RESPIRATION AND HEART RATE. MAY CAUSE FROSTBITE. Avoid breathing gas. Store and use with adequate ventilation. Do not get liquid in eyes, on skin or clothing. Cylinder temperature should not exceed 52oC(125oF). Use equipment rated for cylinder pressure. Use a back flow preventive device in the piping. Close valve after each use and when empty. Use in accordance with Material Safety Data Sheet (MSDS).
FIRST AID: IF INHALED, remove to fresh air. If not breathing, give artificial respiration. If breathing is difficult, give oxygen. Call a physician. IN CASE OF FROSTBITE, obtain medical treatment immediately. CAS: 124-38-9

PACKAGE LABEL

REFRIGERATED LIQUID
CARBON DIOXIDE, REFRIGERATED LIQUID UN2187
Non-Flammable Gas
ALWAYS KEEP CONTAINER IN UPRIGHT POSITION. DO NOT CHANGE OR FORCE FIT CONNECTIONS.
Rx only
CAUTION: Federal law prohibits dispensing without a prescription.
WARNING: Administration of Carbon Dioxide may be hazardous or contraindicated. For use by or under the supervision of a licensed practitioner who is experienced in the use and administration of Carbon Dioxide and is familiar with the indications, effects, dosages, methods, and frequency and duration of administration, and with the hazards, contraindications and side effects, and the precautions to be taken.
WARNING: COLD LIQUID AND GAS UNDER PRESSURE. CAN CAUSE RAPID SUFFOCATION. CAN INCREASE RESPIRATION AND HEART RATE. MAY CAUSE FROSTBITE. Avoid breathing gas. Store and use with adequate ventilation. Do not get liquid in eyes, on skin or clothing. Cylinder temperature should not exceed 52oC(125oF). For liquid withdrawal, wear face shield and gloves. Do not drop. Use suitable hand truck for container movement. Close valve after each use and when empty. Use a back flow preventive device in the piping. Use in accordance with Material Safety Data Sheet (MSDS).
FIRST AID: IF INHALED, remove to fresh air. If not breathing, give artificial respiration. If breathing is difficult, give oxygen. Call a physician. IN CASE OF FROSTBITE, obtain medical treatment immediately. CAS: 124-38-9
DO NOT REMOVE THIS PRODUCT LABEL.